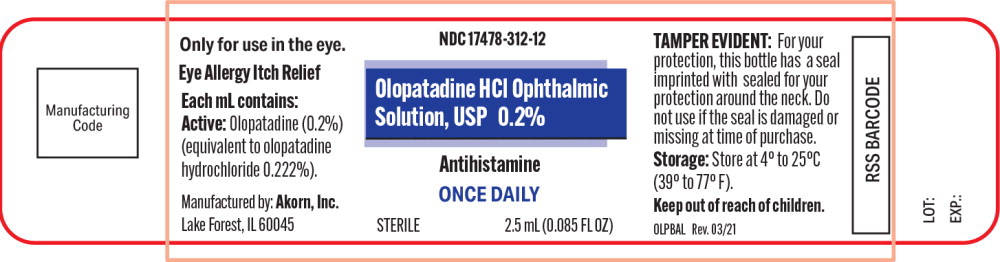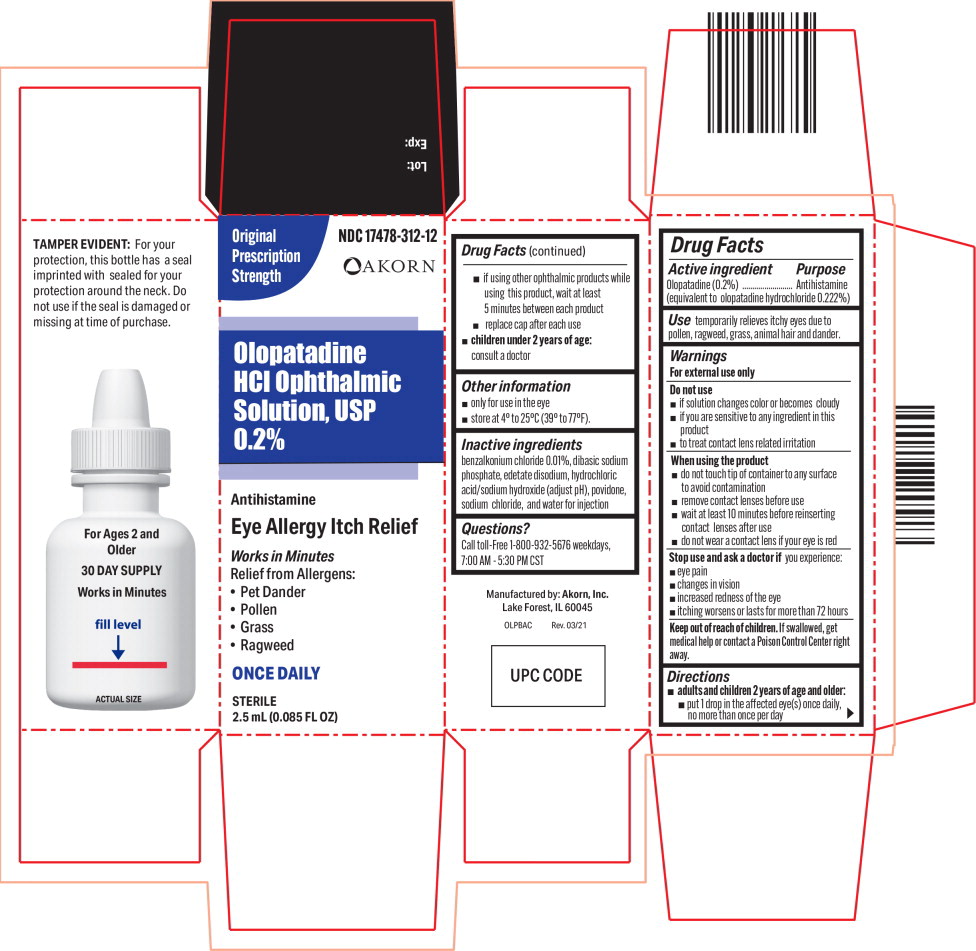 DRUG LABEL: Olopatadine
NDC: 17478-312 | Form: SOLUTION/ DROPS
Manufacturer: Akorn
Category: otc | Type: HUMAN OTC DRUG LABEL
Date: 20220203

ACTIVE INGREDIENTS: Olopatadine Hydrochloride 2 mg/1 mL
INACTIVE INGREDIENTS: benzalkonium chloride; sodium phosphate, dibasic, unspecified form; edetate disodium; hydrochloric acid; sodium hydroxide; povidone, unspecified; sodium chloride; water

Drug Facts

Active ingredient

Olopatadine (0.2%)

(equivalent to olopatadine hydrochloride 0.222%)

Purpose

Antihistamine

Use

temporarily relieves itchy eyes due to pollen, ragweed, grass, animal hair and dander.

Warnings

For external use only

Do not use

- if solution changes color or becomes cloudy
- if you are sensitive to any ingredient in this product
- to treat contact lens related irritation

When using the product

- do not touch tip of container to any surface to avoid contamination
- remove contact lenses before use
- wait at least 10 minutes before reinserting contact lenses after use
- do not wear a contact lens if your eye is red

Stop use and ask a doctor if you experience:

- eye pain
- changes in vision
- increased redness of the eye
- itching worsens or lasts for more than 72 hours

Keep out of reach of children. If swallowed, get medical help or contact a Poison Control Center right away.

Directions

- adults and children 2 years of age and older:
  - put 1 drop in the affected eye(s) once daily, no more than once per day
  - if using other ophthalmic products while using this product, wait at least 5 minutes between each product
  - replace cap after each use
- children under 2 years of age: consult a doctor

Other information

- only for use in the eye
- store at 4° to 25°C (39° to 77°F).

Inactive ingredients

benzalkonium chloride 0.01%, dibasic sodium phosphate, edetate disodium, hydrochloric acid/sodium hydroxide (adjust pH), povidone, sodium chloride, and water for injection

Questions?

Call toll-Free 1-800-932-5676 weekdays, 7:00 AM - 5:30 PM CST

Principal Display Panel Text for Container Label:

NDC 17478-312-12

Olopatadine HCl Ophthalmic

Solution, USP 0.2%

Antihistamine

ONCE DAILY

STERILE 2.5 mL (0.085 FL OZ)

Principal Display Panel Text for Carton Label:

Original NDC 17478-312-12

Prescription

Strength Akorn logo

Olopatadine

HCl Ophthalmic

Solution, USP

0.2%

Antihistamine

Eye Allergy Itch Relief

Works in Minutes

Relief from Allergens:

• Pet Dander

• Pollen

• Grass

• Ragweed

ONCE DAILY

STERILE

2.5 mL (0.085 FL OZ)